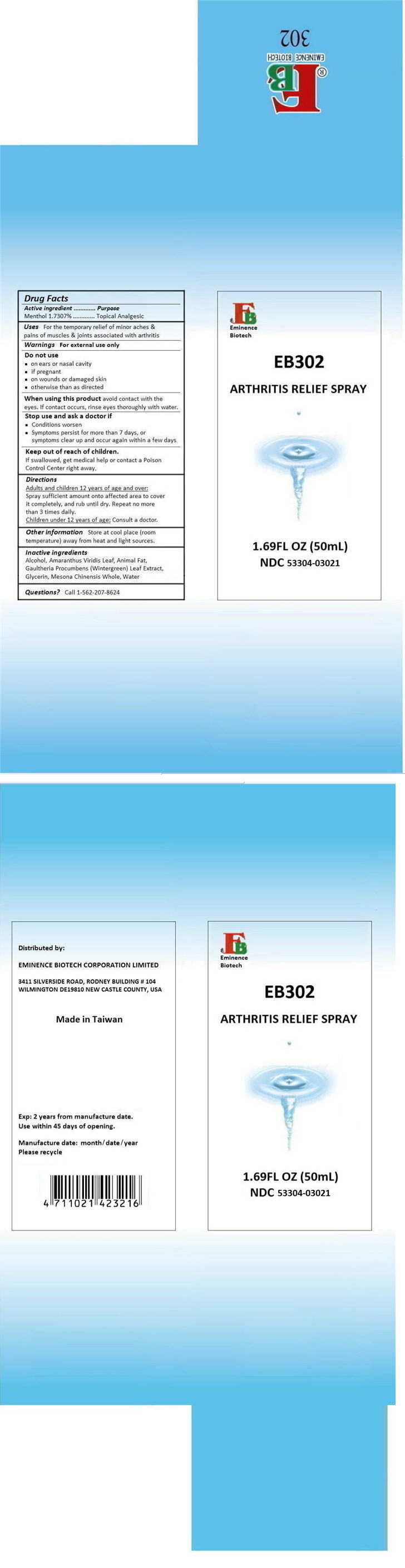 DRUG LABEL: EB302 ARTHRITIS RELIEF
NDC: 53304-0302 | Form: SPRAY
Manufacturer: EMINENCE BIOTECH CORPORATION LIMITED
Category: otc | Type: HUMAN OTC DRUG LABEL
Date: 20180320

ACTIVE INGREDIENTS: MENTHOL, UNSPECIFIED FORM 865.4 mg/50 mL
INACTIVE INGREDIENTS: ALCOHOL; AMARANTHUS VIRIDIS LEAF; PORK SIDE BACON, CURED FAT; GAULTHERIA PROCUMBENS LEAF; GLYCERIN; PLATOSTOMA PALUSTRE WHOLE; WATER

EB302 ARTHRITIS RELIEF

Drug Facts

Active ingredient

Menthol 1.7307%

Purpose

Topical Analgesic

Uses

For the temporary relief of minor aches & pains of muscles & joints associated with arthritis

Warnings

For external use only

Do not use

- on ears or nasal cavity
- if pregnant
- on wounds or damaged skin
- otherwise than as directed

When using this product avoid contact with the eyes. If contact occurs, rinse eyes thoroughly with water.

Stop use and ask a doctor if

- Conditions worsen
- Symptoms persist for more than 7 days, or symptoms clear up and occur again within a few days

Keep out of reach of children.

If swallowed, get medical help or contact a Poison Control Center right away.

Directions

Adults and children 12 years of age and over

Spray sufficient amount onto affected area to cover it completely, and rub until dry. Repeat no more than 3 times daily.

Children under 12 years of age

Consult a doctor.

Other information

Store at cool place (room temperature) away from heat and light sources.

Inactive ingredients

Alcohol, Amaranthus Viridis Leaf, Animal Fat, Gaultheria Procumbens (Wintergreen) Leaf Extract, Glycerin, Mesona Chinensis Whole, Water

Questions?

Call 1-562-207-8624

Distributed by:

EMINENCE BIOTECH CORPORATION LIMITED

3411 SILVERSIDE ROAD, RODNEY BUILDING # 104
WILMINGTON DE19810 NEW CASTLE COUNTY, USA

PRINCIPAL DISPLAY PANEL - 50mL Bottle Carton

EB
Eminence
Biotech

EB302

ARTHRITIS RELIEF SPRAY

1.69FL OZ (50mL)
NDC 53304-03021